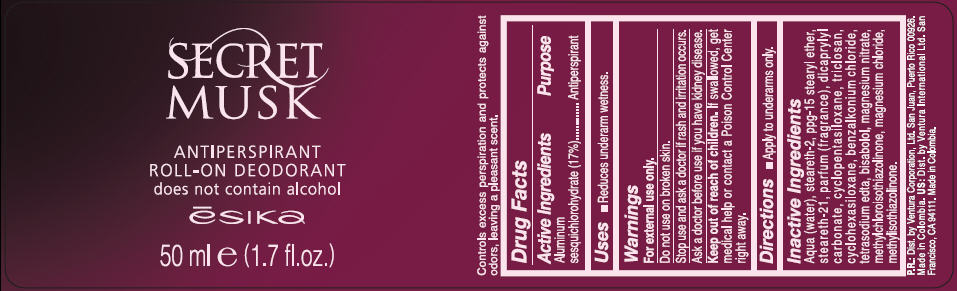 DRUG LABEL: ESIKA 
NDC: 13537-139 | Form: LIQUID
Manufacturer: Ventura Corporation Ltd.
Category: otc | Type: HUMAN OTC DRUG LABEL
Date: 20111215

ACTIVE INGREDIENTS: Aluminum Sesquichlorohydrate 0.17 g/1 mL
INACTIVE INGREDIENTS: water; steareth-2; steareth-21; dicaprylyl carbonate; cyclomethicone 5; triclosan; cyclomethicone 6; benzalkonium chloride; edetate sodium; levomenol; magnesium nitrate; methylchloroisothiazolinone; magnesium chloride; methylisothiazolinone

SECRET
MUSK
ANTIPERSPIRANT
ROLL-ON DEODORANT

Drug Facts

Active Ingredients

Aluminum sesquichlorohydrate (17%)

Purpose

Antiperspirant

Uses

- reduces underarm wetness.

Warnings

- For external use only.

- Do not use on broken skin.

- Stop use and ask a doctor if rash and irritation occurs.

- Ask a doctor before use if you have kidney disease.

- Keep out of reach of children. If swallowed, get medical help or contact a Poison Control Center right away.

Directions

- apply to underarms only.

Inactive ingredients

Aqua (water), steareth-2, ppg-15 stearyl ether, steareth-21, fragrance, dicaprylyl carbonate, cyclopentasiloxane, triclosan, cyclohexasiloxane, benzalkonium chloride, tetrasodium edta, bisabolol, magnesium nitrate, methylchloroisothiazolinone, magnesium chloride, methylisothiazolinone.

PR: Distributed by Ventura Corporation, Ltd. San Juan, Puerto Rico 00926.

PRINCIPAL DISPLAY PANEL - 50 ml Bottle Label

SECRET
MUSK

ANTIPERSPIRANT
ROLL-ON DEODORANT
does not contain alcohol

ēsika

50 ml e (1.7 fl.oz.)